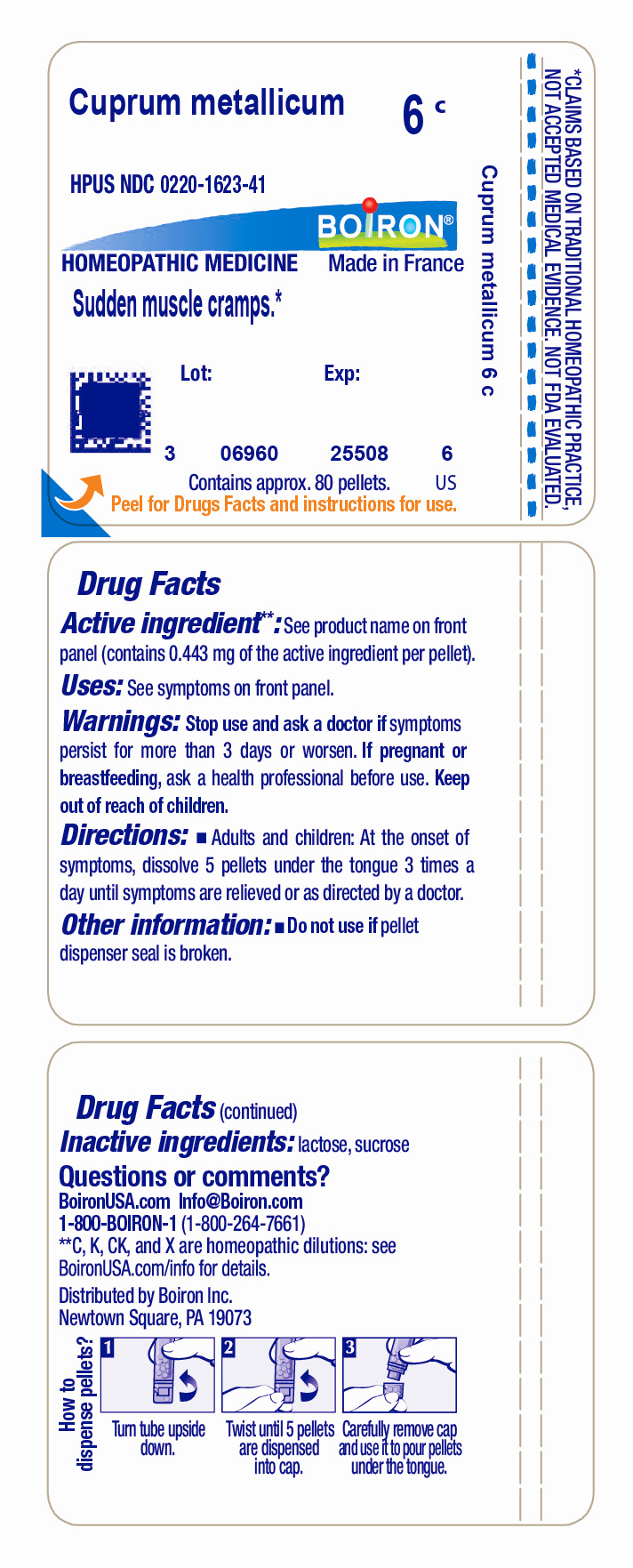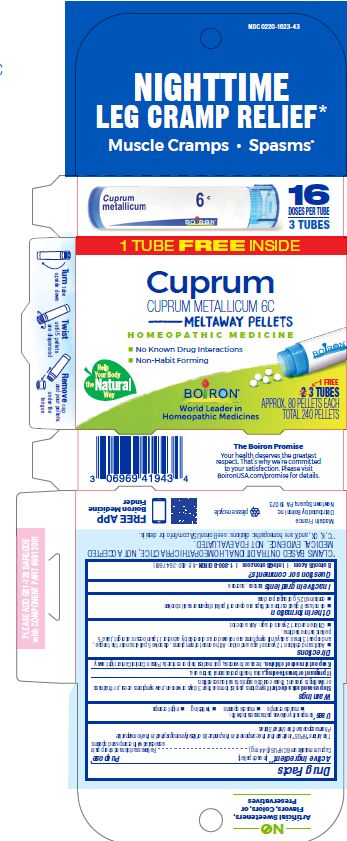 DRUG LABEL: Cuprum metallicum
NDC: 0220-1623 | Form: PELLET
Manufacturer: Boiron
Category: homeopathic | Type: HUMAN OTC DRUG LABEL
Date: 20230120

ACTIVE INGREDIENTS: COPPER 6 [hp_C]/6 [hp_C]
INACTIVE INGREDIENTS: LACTOSE, UNSPECIFIED FORM; SUCROSE

Cuprum metallicum 6C

Active ingredient** (in each pellet)

Cuprum metallicum 6C HPUS (0.44 mg)

The letters "HPUS" indicate that the component in this product is officially monographed in the Homeopathic Pharmacopoeia of the United States.

Purpose*

Cuprum metallicum 6C HPUS (0.44 mg) .... Relieves sudden and sharp pain associated with cramps and spasms

Uses*

Tube - Sudden muscle cramps*

Box - temporarily relieves pain associated with:

- muscle cramps
- muscle spasms
- twitching
- night cramps

STOP USE

Tube - Stop use and ask a doctor if symptoms persist for more than 3 days or worsen

Box - Stop use and ask a doctor if symptoms persist for more than 3 days or worsen, new symptoms occur, or if redness or swelling is present. These could be signs of a serious condition.

PREGNANCY OR BREAST FEEDING

If pregnant or breastfeeding, ask a health professional before use.

Tube - Keep out of reach of children

Box - Keep out of reach of children. In case of overdose, get medical help or contact a Poison Control Center right away.

DOSAGE AND ADMINISTRATION

Tube - Adults and children: At the onset of symptoms, dissolve 5 pellets under the tongue 3 times a day until symptoms are relieved or as directed by a doctor.

Box - Adults and children 12 years of age and older: At the onset of symptoms, dissolve 5 pellets under the tongue, and repeat 3 times a day until symptoms are relieved or as directed by a doctor. If pain occurs at night, take 5 pellets before bedtime.

Children under 12 years of age: Ask a doctor.

INACTIVE INGREDIENT

lactose, sucrose

do not use if glued carton end flaps are open or if pellet dispenser seal is broken

contains 0.25 g of sugar per dose

3 TUBES

APPROX. 80 PELLETS EACH

TOTAL 240 PELLETS

16 DOSES PER TUBE

Nighttime Leg Cramp Relief*

Muscle Cramps Spasms*

Turn tube upside down. Twist until 5 pellets are dispensed. Remove cap and pour pellets under the tongue.

*CLAIMS BASED ON TRADITIONAL HOMEOPATHIC PRACTICE NOT ACCEPTED MEDICAL EVIDENCE. NOT FDA EVALUATED.
*C,K,CK, and X are homeopathic dilutions: see BoironUSA.com/info for details.

Tube

Do not use if pellet dispenser seal is broken.
Contains approx 80 pellets.
How to dispense pellets? Turn tube upside down. Twist until 5 pellets are dispensed into cap. Carefully remove the cap and use it to pour pellets under the tongue.

QUESTIONS

1-800-BOIRON-1 (1-800-264-7661),
BoironUSA.com Info@boiron.com

Made in France
Distributed by Boiron, Inc. Newtown Square, PA 19073